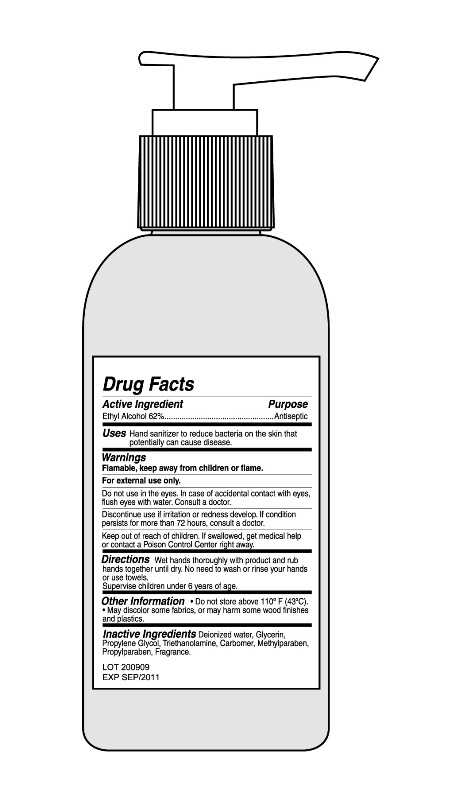 DRUG LABEL: HAND SANITIZER 
NDC: 50260-200 | Form: GEL
Manufacturer: Fercy Personal Care Products Co Limited
Category: otc | Type: HUMAN OTC DRUG LABEL
Date: 20100201

ACTIVE INGREDIENTS: ALCOHOL  62 mL/100 mL
INACTIVE INGREDIENTS: WATER 31.1 mL/100 mL; GLYCERIN 2 mL/100 mL; PROPYLENE GLYCOL 2 mL/100 mL; TROLAMINE 1 mL/100 mL; CARBOMER  934 0.9 mL/100 mL; Methylparaben 0.5 mL/100 mL; Propylparaben 0.5 mL/100 mL

Drug Fact

Active Ingredient

Ethyl Alcohol 62%

Purpose

Antiseptic

Uses

Hand sanitizer to reduce bacteria on the skin that potentially can cause disease

Warning

Flamable, keep away from children or flame.

For external use only.
Do not use in the eyes.In case of accidental contact with eyes,
flush eyes with water. Consult a doctor.
Discontinue use if irritation or redness develop.If condition
persists for more than 72 hours,consult a doctor.
Keep out of reach of children.If swallowed, get medical help
or contact a Poison Control Center right away.

Directions

Wet hands thoroughly with product and rub hands together until dry. No need to wash or rinse your hands
or use towels.
Supervise children under 6 years of age.

Other Information

·Do not store above 110 oF(43 oC).
·May discolor some fabrics, or may ham some wood finishes
and plastics.
Deionized water,Glycerin,Propylene Glycol,Triethanolamine,Carbomer,Methylparaben,Propylparaben,Fragrance.

PACKAGE LABEL

Enter section text here